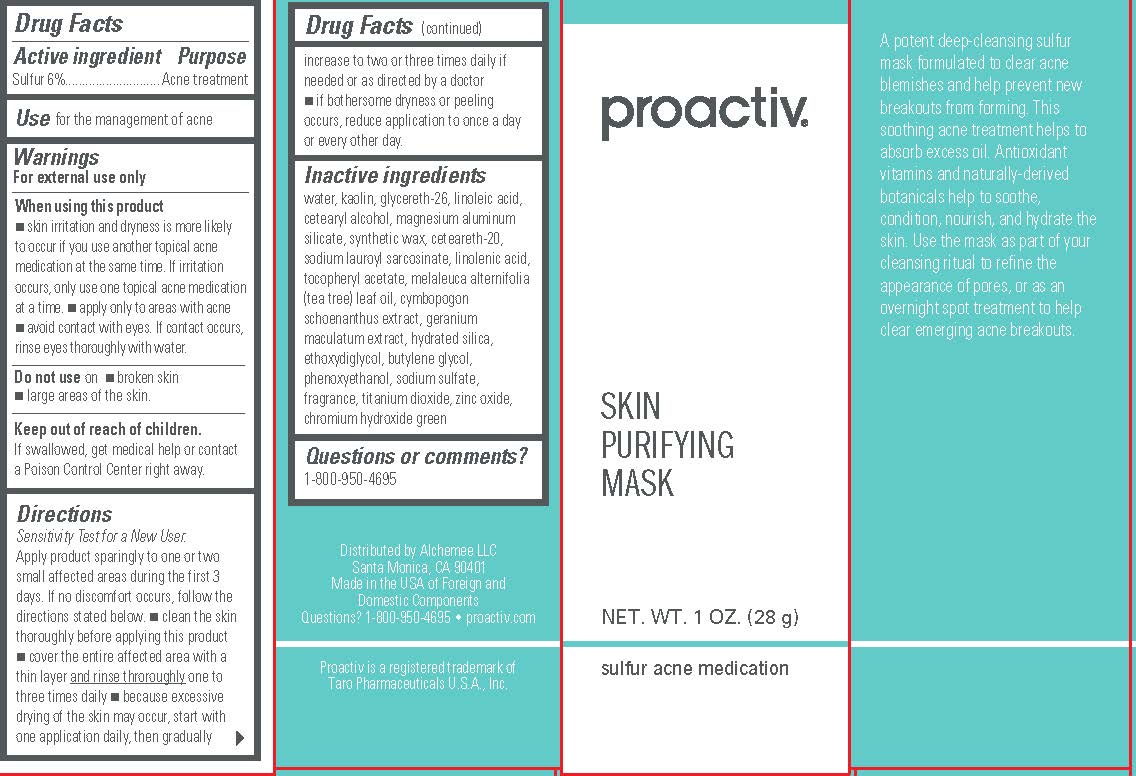 DRUG LABEL: Proactiv Skin Purifying Mask
NDC: 11410-013 | Form: LOTION
Manufacturer: THE PROACTIV COMPANY LLC
Category: otc | Type: HUMAN OTC DRUG LABEL
Date: 20260107

ACTIVE INGREDIENTS: SULFUR 6 g/100 g
INACTIVE INGREDIENTS: WATER; KAOLIN; GLYCERETH-26; LINOLEIC ACID; CETOSTEARYL ALCOHOL; MAGNESIUM ALUMINUM SILICATE; SYNTHETIC WAX (1200 MW); POLYOXYL 20 CETOSTEARYL ETHER; SODIUM LAUROYL SARCOSINATE; LINOLENIC ACID; .ALPHA.-TOCOPHEROL ACETATE; TEA TREE OIL; CYMBOPOGON SCHOENANTHUS TOP; GERANIUM MACULATUM ROOT; HYDRATED SILICA; DIETHYLENE GLYCOL MONOETHYL ETHER; SODIUM SULFATE; BUTYLENE GLYCOL; PHENOXYETHANOL; TITANIUM DIOXIDE; ZINC OXIDE; CHROMIUM HYDROXIDE GREEN

Proactiv Skin Purifying Mask

Drug Facts

Active ingredient

Sulfur 6%

Purpose

Acne treatment

Use

for the management of acne

Warnings

For external use only

When using this product

- skin irritation and dryness is more likely to occur if you use another topical acne medication at the same time. If irritation occurs, only use one topical acne medication at a time.
- apply only to areas with acne
- avoid contact with eyes. If contact occurs, rinse eyes thoroughly with water.

Do not useon

- broken skin
- large areas of the skin

Keep out of reach of children.

If swallowed, get medical help or contact a Poison Control Center right away.

Directions

- Sensitivity Test for a New User . Apply product sparingly to one or two small affected areas during the first 3 days. If no discomfort occurs, follows the directions stated below.
- clean the skin thoroughly before applying this product
- cover the entire affected area with a thin layer and rinse thoroughlyone to three times daily
- because excessive drying of the skin may occur, start with one application daily, then gradually increase to two or three times daily if needed or as directed by a doctor
- if bothersome dryness or peeling occurs, reduce application to once a day or every other day.

Inactive ingredients

water, kaolin, glycereth-26, linoleic acid, cetearyl alcohol, magnesium aluminum silicate, synthetic wax, ceteareth-20, sodium lauroyl sarcosinate, linolenic acid, tocopheryl acetate, melaleuca alternifolia (tea tree) leaf oil, cymbopogon schoenanthus extract, geranium maculatum extract, hydrated silica, ethoxydiglycol, butylene glycol, phenoxyethanol, sodium sulfate, fragrance, titanium dioxide, zinc oxide, chromium hydroxide green

Questions or comments?

1-800-950-4695

Distributed by Alchemee LLC
Santa Monica, CA 90401
Made in the USA of Foreign and
Domestic Components
Questions? 1-800-950-4695 • proactiv.com
Proactiv is a registered trademark of
Taro Pharmaceuticals U.S.A., Inc.

PRINCIPAL DISPLAY PANEL - 1 OZ. 28 g

proactiv®

SKIN
PURIFYING
MASK

NET. WT. 1 OZ. (28 g)
sulfur acne medication